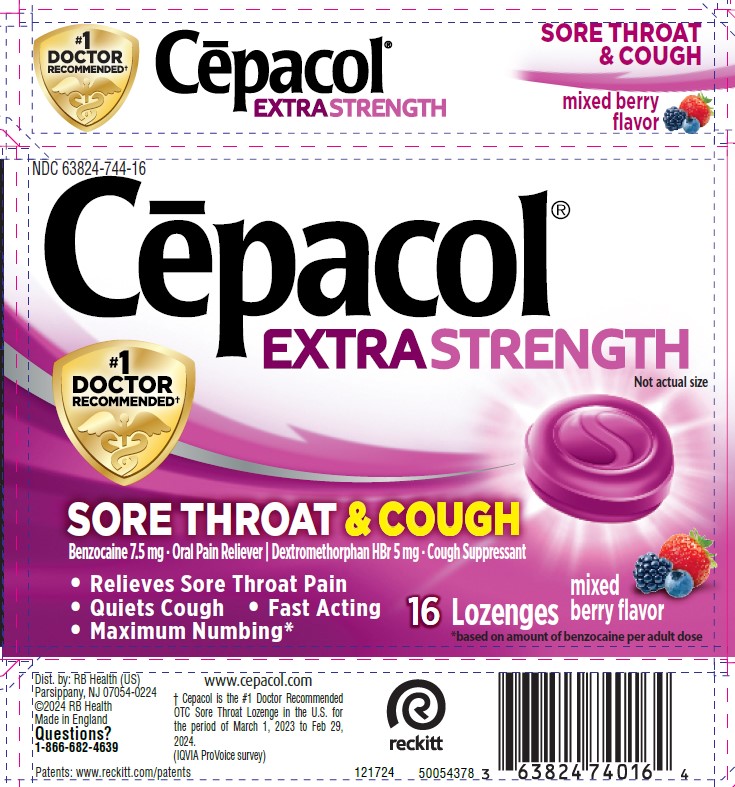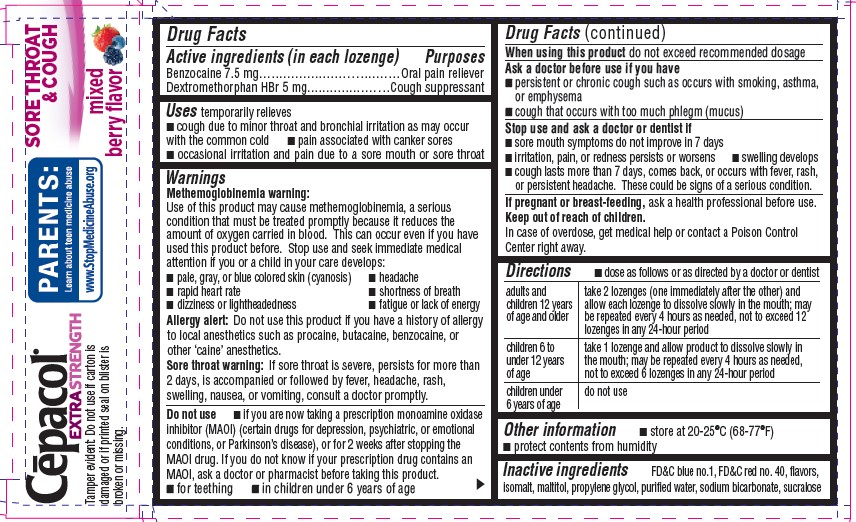 DRUG LABEL: Cepacol
NDC: 63824-744 | Form: LOZENGE
Manufacturer: RB Health (US) LLC
Category: otc | Type: HUMAN OTC DRUG LABEL
Date: 20250321

ACTIVE INGREDIENTS: DEXTROMETHORPHAN HYDROBROMIDE 5 mg/1 1; BENZOCAINE 7.5 mg/1 1
INACTIVE INGREDIENTS: FD&C BLUE NO. 1; FD&C RED NO. 40; ISOMALT; MALTITOL; PROPYLENE GLYCOL; WATER; SODIUM BICARBONATE; SUCRALOSE

Cēpacol®
Extra Strength Sore Throat & Cough

Drug Facts

ACTIVE INGREDIENT

PURPOSE

Active ingredients (in each lozenge) | Purposes
Benzocaine 7.5 mg | Oral pain reliever
Dextromethorphan HBr 5 mg | Cough suppressant

Uses

temporarily relieves

- cough due to minor throat and bronchial irritation as may occur with the common cold
- pain associated with canker sores
- occasional irritation and pain due to a sore mouth or sore throat

Warnings

Methemoglobinemia warning

Use of this product may cause methemoglobinemia, a serious condition that must be treated promptly because it reduces the amount of oxygen carried in blood. This can occur even if you have used this product before. Stop use and seek immediate medical attention if you or a child in your care develops:

- pale, gray, or blue colored skin (cyanosis)
- headache
- rapid heart rate
- shortness of breath
- dizziness or lightheadedness
- fatigue or lack of energy

Allergy alert

Do not use this product if you have a history of allergy to local anesthetics such as procaine, butacaine, benzocaine, or other 'caine' anesthetics.

Sore throat warning

If sore throat is severe, persists for more than 2 days, is accompanied or followed by fever, headache, rash, swelling, nausea, or vomiting, consult a doctor promptly.

Do not use

- if you are now taking a prescription monoamine oxidase inhibitor (MAOI) (certain drugs for depression, psychiatric, or emotional conditions, or Parkinson's disease), or for 2 weeks after stopping the MAOI drug. If you do not know if your prescription drug contains an MAOI, ask a doctor or pharmacist before taking this product.
- for teething
- in children under 6 years of age

Ask a doctor before use if you have

- persistent or chronic cough such as occurs with smoking, asthma, or emphysema
- cough that occurs with too much phlegm (mucus)

Stop use and ask a doctor or dentist if

- sore mouth symptoms do not improve in 7 days
- irritation, pain, or redness persists or worsens
- swelling develops
- cough lasts more than 7 days, comes back, or occurs with fever, rash, or persistent headache. These could be signs of a serious condition.

PREGNANCY OR BREAST FEEDING

If pregnant or breast-feeding,ask a health professional before use.

Keep out of reach of children.

In case of overdose, get medical help or contact a Poison Control Center right away.

Do not exceed recommended dosage.

Directions

adults and children 12 years of age and older | take 2 lozenges (one immediately after the other) and allow each lozenge to dissolve slowly in the mouth; may be repeated every 4 hours as needed, not to exceed 12 lozenges in 24 hours, or as directed by a doctor or dentist
children 6 to under 12 years of age | take 1 lozenge and allow product to dissolve slowly in the mouth; may be repeated every 4 hours as needed, not to exceed 6 lozenges in 24 hours, or as directed by a doctor or dentist
children under 6 years of age | do not use

Other information

- store at 20-25°C (68-77°F)
- protect contents from humidity

Inactive ingredients

FD&C blue no. 1, FD&C red no. 40, flavors, isomalt, purified water, sucralose

Questions?

1-866-682-4639

Dist. by: RB Health (US)
Parsippany, NJ 07054-0224

PRINCIPAL DISPLAY PANEL - 16 Lozenge Blister Pack Carton

NDC 63824-744-16

Cēpacol®
EXTRA STRENGTH

#1
DOCTOR
RECOMMENDED†

SORE THROAT & COUGH
Benzocaine 7.5 mg Oral Pain Reliever | Dextromethorphan HBr 5 mg Cough Suppressant

- Relieves Sore Throat Pain
- Quiets Cough • Fast Acting
- Maximum Numbing*

16 Lozenges mixed berry flavor
*based on amount of benzocaine per adult dose